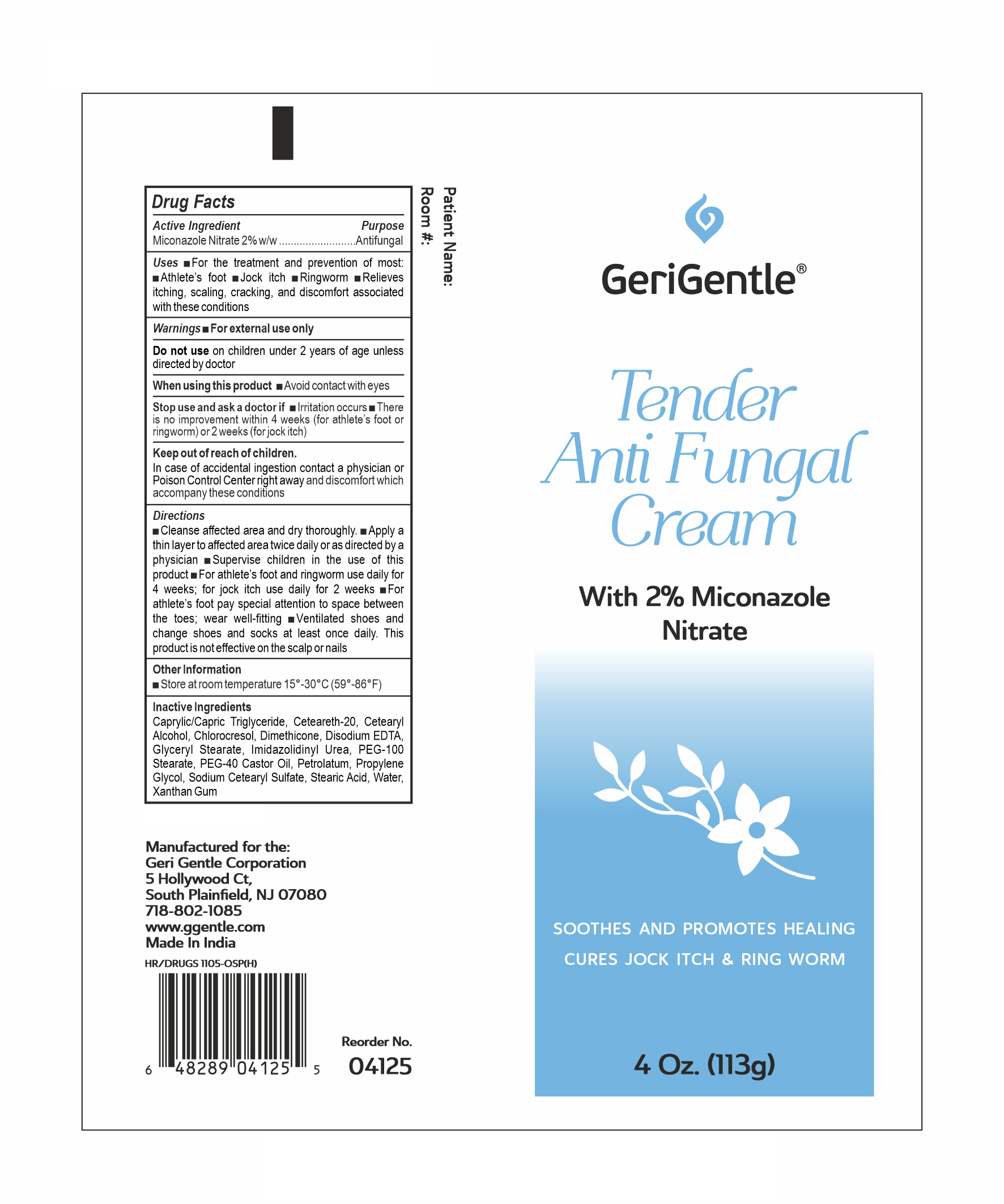 DRUG LABEL: MICONAZOLE Nitrate 2% Cream ANTIFUNGAL
NDC: 69771-041 | Form: CREAM
Manufacturer: GERI-GENTLE CORPORATION
Category: otc | Type: HUMAN OTC DRUG LABEL
Date: 20250421

ACTIVE INGREDIENTS: MICONAZOLE NITRATE 2 g/100 g
INACTIVE INGREDIENTS: CETOSTEARYL ALCOHOL; DIMETHICONE; EDETATE DISODIUM; PEG-100 STEARATE; WATER; STEARIC ACID; XANTHAN GUM; GLYCERYL MONOSTEARATE; POLYOXYL 20 CETOSTEARYL ETHER; CHLOROCRESOL; PROPYLENE GLYCOL; SODIUM CETOSTEARYL SULFATE; IMIDUREA; PEG-40 CASTOR OIL; PETROLATUM; CAPRYLIC/CAPRIC/LAURIC TRIGLYCERIDE

MICONAZOLE Nitrate 2% Cream ANTIFUNGAL

Active ingredient

Miconazole Nitrate 2% w/w

Purpose

Anti-Fungal

Uses

- For the treatment and prevention of most athlete's foot (tinea pedis), jock itch (tinea crurus), and ringworm (tinea capitis)
- relieves itching, scaling, cracking, burning and discomfort associated with these conditions.

Warnings

For external use only

DO NOT USE

on children under 2 years of age unless directed by Doctor

When using this product

Avoid contact with eyes

Stop use and ask a doctor if

irritation occurs

there is no improvement within 4 weeks (for athlete's foot or ringworm) or 2 weeks (for jock itch)

Keep out of reach of children

In case of accidental ingestion contact a physician or Poison Control Center right away and discomfort which accompany these conditions

Directions

Clean the affected area and dry thoroughly • Apply a thin layer of the product over affected area twice daily (morning and night) or as directed by a healthcare professional • Supervise children in the use of this product.

For athlete's foot: • Use daily for 4 weeks. If condition persists, consult a healthcare professional. • Pay special attention to the spaces between the toes • Wear well fitting, ventilated shoes • Change socks atleast once daily.

For ringworm: Use daily for 4 weeks. If condition persists, consult a healthcare professional.

For jock itch:Use daily for 2 weeks. If condition persists longer, consult a healthcare professional.

This product is not effective on the scalp or nails.

Other Information

• Store at 15° - 30° c (59° - 86° f)

INACTIVE INGREDIENT

Caprylic/capric triglyceride, Cetereath-20, Cetearyl Alcohol, Chlorocresol, Dimethicone, Disodium EDTA, Glyceryl Stearate, Imidazolidinyl Urea, PEG-100 Stearate, PEG-40 Castor Oil, Petrolatum, Propylene Glycol, Sodium Cetearyl Sulfate, Stearic Acid, Water, Xanthum Gum